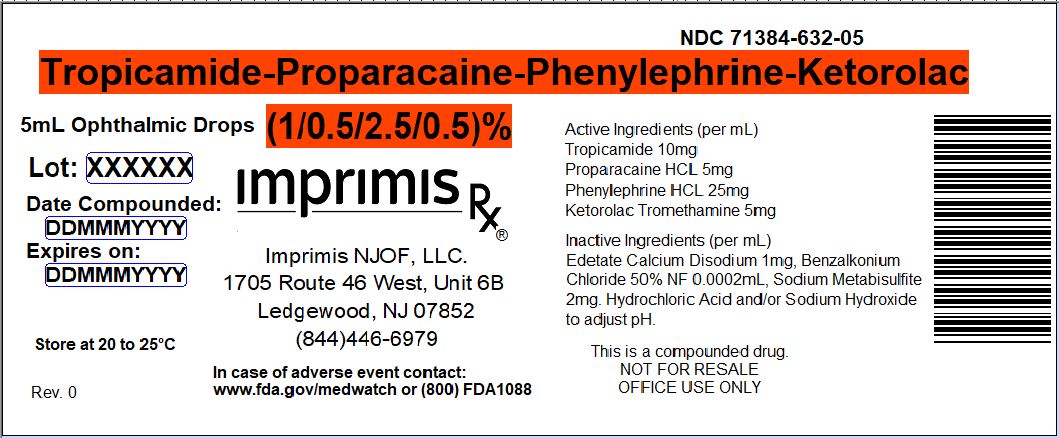 DRUG LABEL: Mydriatic-4
NDC: 71384-632 | Form: SOLUTION/ DROPS
Manufacturer: Imprimis NJOF, LLC
Category: prescription | Type: HUMAN PRESCRIPTION DRUG LABEL
Date: 20180501

ACTIVE INGREDIENTS: TROPICAMIDE 10 mg/1 mL; KETOROLAC TROMETHAMINE 5 mg/1 mL; PROPARACAINE HYDROCHLORIDE 5 mg/1 mL; PHENYLEPHRINE HYDROCHLORIDE 25 mg/1 mL

STORAGE AND HANDLING

Store at 20° to 25° C (68° to 77° F)